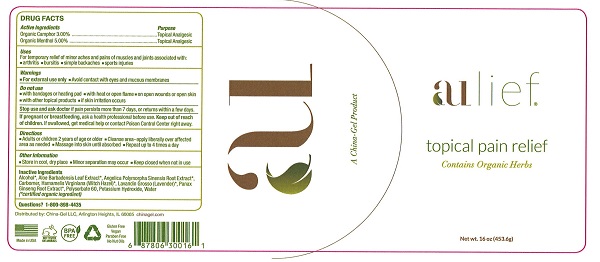 DRUG LABEL: Aulief
NDC: 76305-302 | Form: CREAM
Manufacturer: China-Gel, LLC
Category: otc | Type: HUMAN OTC DRUG LABEL
Date: 20251104

ACTIVE INGREDIENTS: CAMPHOR (NATURAL) 30 mg/1 g; MENTHOL 50 mg/1 g
INACTIVE INGREDIENTS: LAVANDIN OIL; POLYSORBATE 60; WITCH HAZEL; ALCOHOL; PANAX GINSENG ROOT OIL; WATER; POTASSIUM HYDROXIDE; ANGELICA POLYMORPHA ROOT; ALOE VERA LEAF; CARBOMER 980

Aulief Topical Pain Reliever

Active Ingredients

Organic Camphor 3.00%

Organic Menthol 5.00%

Purpose

Topical Analgesic

Topical Analgesic

Uses

For temporary relief of minor aches and pains of muscles and joints associated with:

- arthritis
- bursitis
- simple backache
- sports injuries

Warnings

- For external use only
- Avoid contact with eyes and mucous membranes

Do not use

- with bandages or heating pad
- with heat or open flame
- on open wounds or open skin
- with other topical products
- if skin irritation occurs

Stop use and ask a doctor if pain persists more than 7 days, or returns within a few days

PREGNANCY OR BREAST FEEDING

If pregnant or breastfeeding, ask a health professional before use.

Keep out of reach of children. If swallowed, get medical help or contact Poison Control Center right away.

Directions

- Adults or children 2 years of age or older
- Cleanse the area-apply liberally over affected area as needed
- Massage into skin until absorbed
- Repeat up to 4 times a day

Other Information

- Store in cool, dry place
- Minor separation may occur
- Keep closed when not in use

Inactive Ingredients

Alcohol*, Aloe Barbadensis, Leaf Extract*, Angelica Polymorpha Sinensis Root Extract*, Carbomer, Hamamelis Virginiana (Witch Hazel)*, Lavandin Grosso (lavender)*, Panex Ginseng Root Extract*, Polysorbate 60, Potassium Hydroxide, Water

(*certified organic ingredient)

Questions?

1-800-898-4435

Principal Display

aulief®

topical pain relief

Contains Organic Herbs

Net Wt. 16oz. (453.6g)